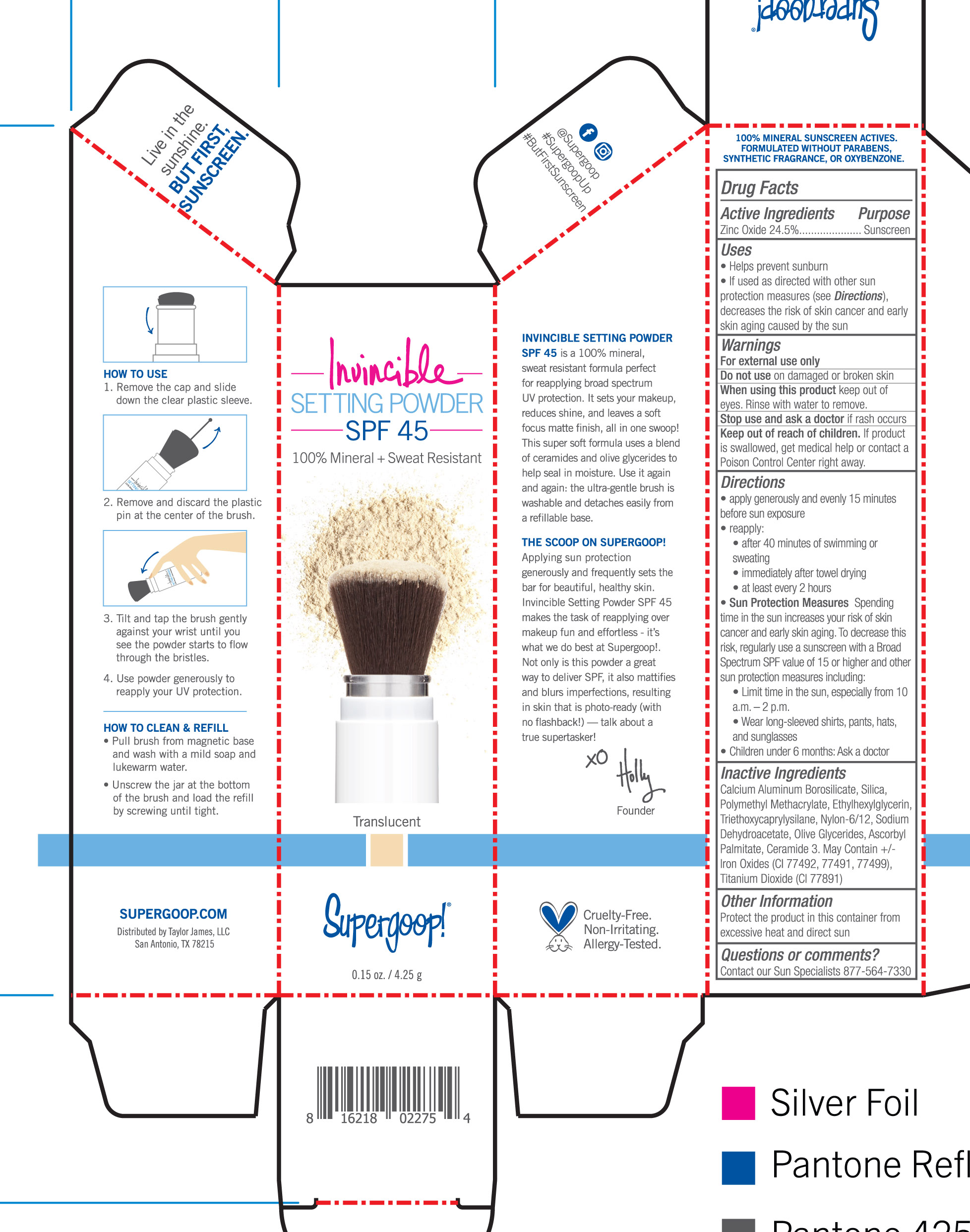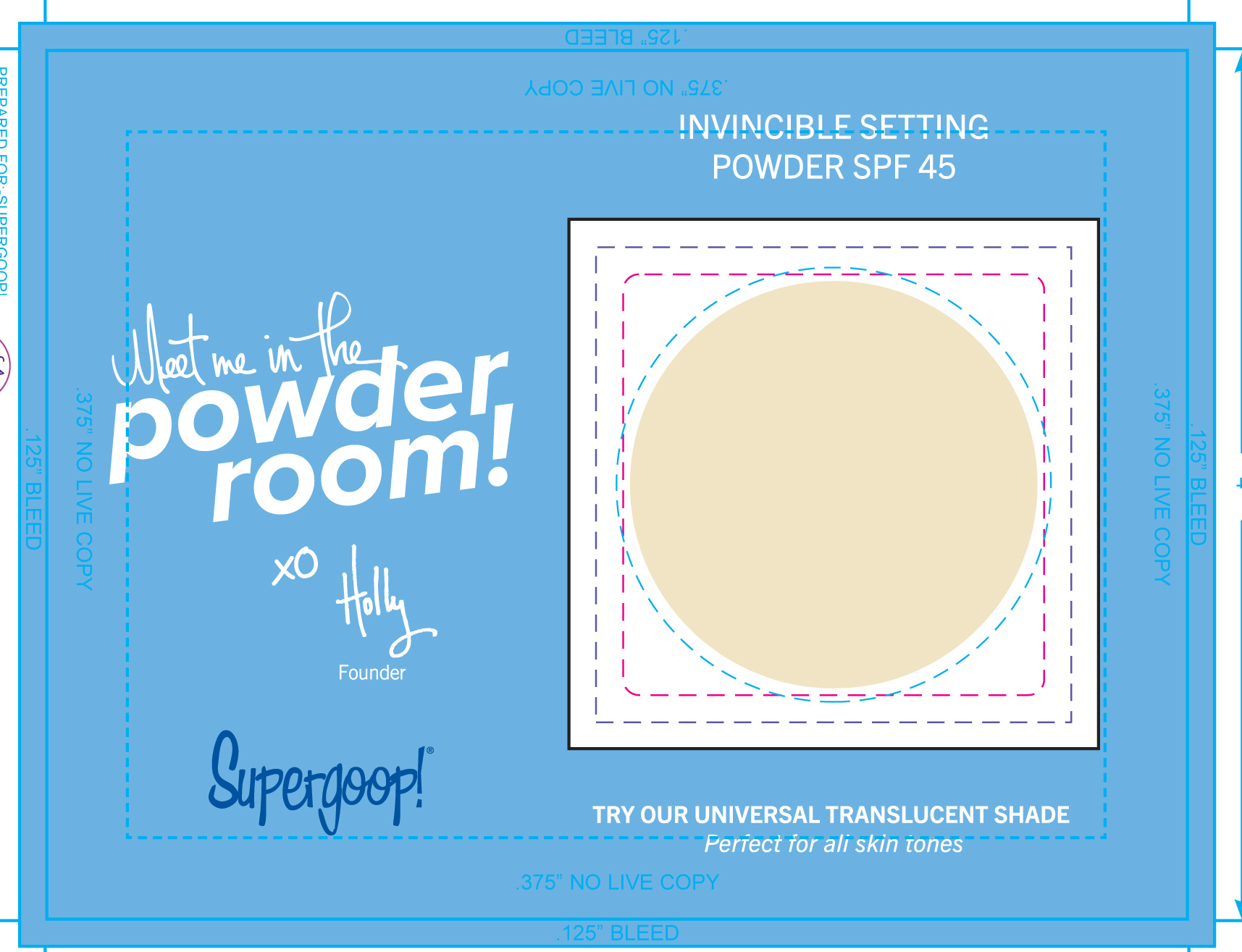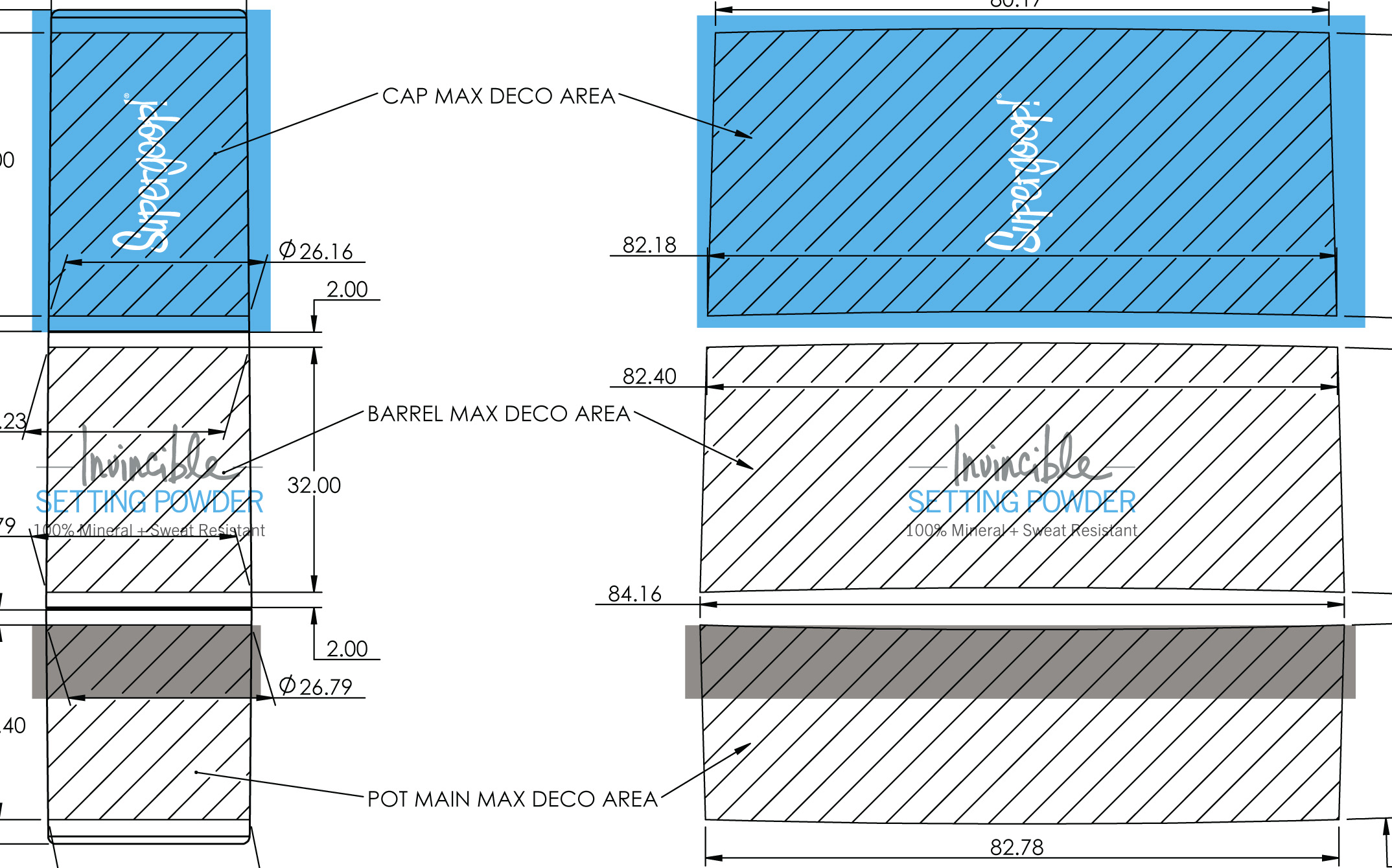 DRUG LABEL: Invincible Setting Powder SPF 45 Translucent
NDC: 75936-145 | Form: POWDER
Manufacturer: TAYLOR JAMES, LTD.
Category: otc | Type: HUMAN OTC DRUG LABEL
Date: 20180212

ACTIVE INGREDIENTS: ZINC OXIDE 24.5 g/100 g
INACTIVE INGREDIENTS: CALCIUM ALUMINUM BOROSILICATE; SILICON DIOXIDE; POLY(METHYL METHACRYLATE; 450000 MW); ETHYLHEXYLGLYCERIN; TRIETHOXYCAPRYLYLSILANE; SODIUM DEHYDROACETATE; ASCORBYL PALMITATE; CERAMIDE 3

Invincible Setting Powder SPF 45 Translucent

Active ingredients Purpose

Zinc Oxide 24.5% Sunscreen

Uses

- Helps Prevent Sunburn

- If used as directed with other sun protection measures (see Directions), decreases the risk of skin cancer and early skin aging caused by the sun.

Keep out of reach of children. If product is swallowed, get medical help or contact a Poison Control Center right away.

Stop use and ask a doctor if rash occurs

Warnings

For external use only

Do not use on damaged or broken skin

When using this product keep out of eyes. Rinse with water to remove.

Directions

- apply generously and evenly 15 minutes before sun exposure

- reapply
- after 40 minutes of swimming or sweating
- immediately after towel drying
- at least every 2 hours
- Sun Protection Measures Spending time in the sun increases your risk of skin cancer and early skin aging. To decrease this risk, regularly use a sunscreen with a Broad Spectrum value of 15 or higher and other sun protections measures including:
- Limit time in the sun, especially from 10a.m. -2p.m.
- Wear long-sleeved shirts, pants, hats, and sunglasses
- Children under 6 months: Ask a doctor

Inactive Ingredients

Calcium Aluminum Borosilicate, Silica, Polymethyl Methacrylate, Ethylhexylglycerin, Triethoxycaprylysilane, Nylon-6/12, Sodium Dehydroacetate, Olive Glycerides, Ascorbyl Palmitate, Ceramide 3. May contain +/- Iron Oxides (CI 77492, CI 77491, CI 77499), Titanium Dioxide (CI 77891)

PACKAGE LABEL

Invincible Setting Powder SPF 45

100% Mineral + Sweat resistant

Translucent

0.15 oz./ 4.25 g